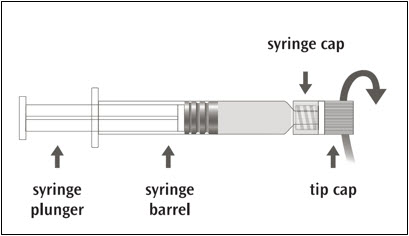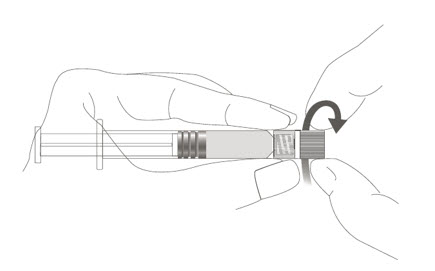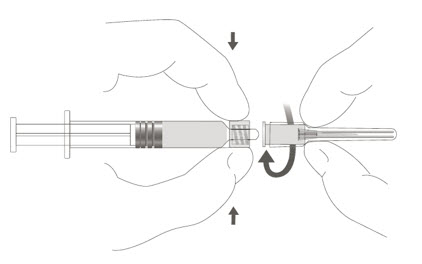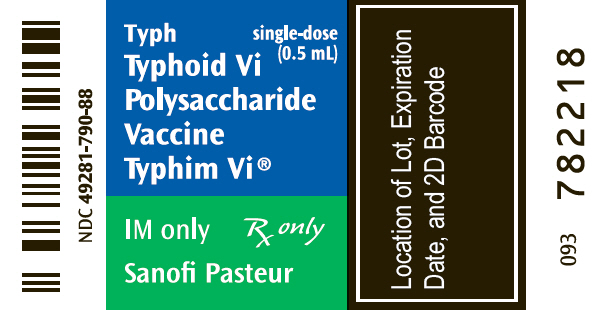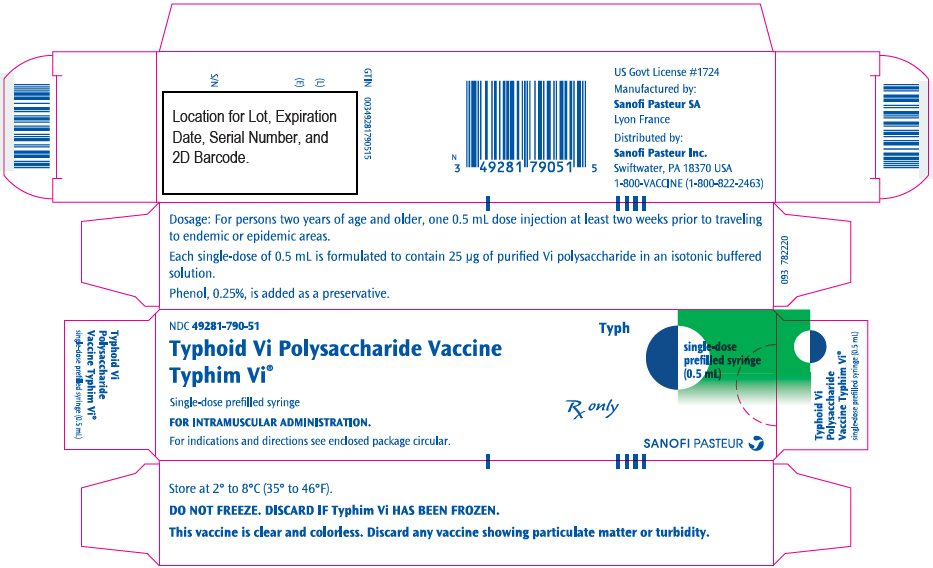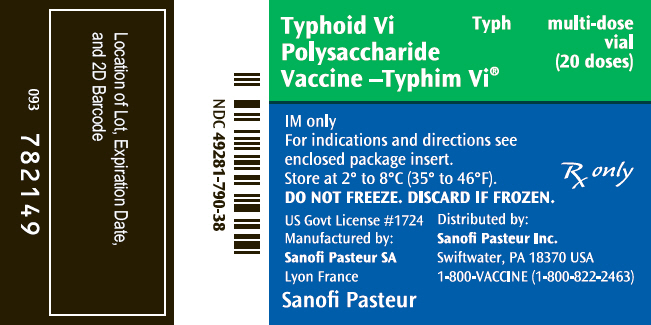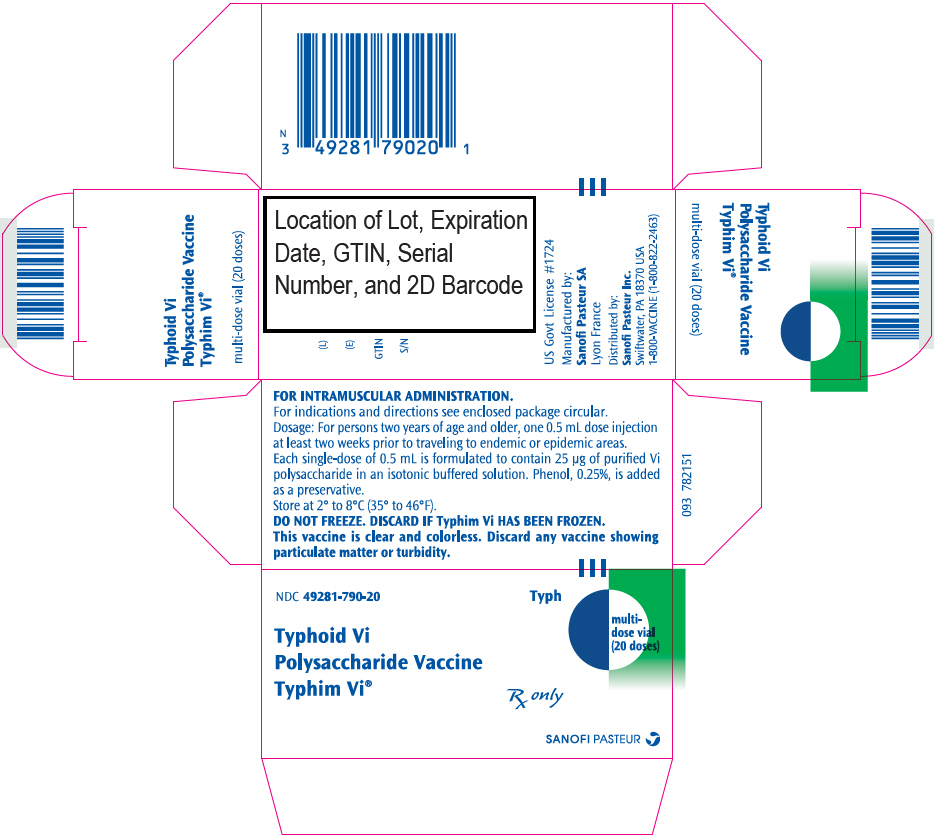 DRUG LABEL: Typhim Vi
NDC: 49281-790 | Form: INJECTION, SOLUTION
Manufacturer: Sanofi Vaccines US Inc.
Category: other | Type: VACCINE LABEL
Date: 20260212

ACTIVE INGREDIENTS: SALMONELLA TYPHI TY2 VI POLYSACCHARIDE ANTIGEN 25 ug/0.5 mL
INACTIVE INGREDIENTS: SODIUM CHLORIDE 4.15 mg/0.5 mL; SODIUM PHOSPHATE, DIBASIC, DIHYDRATE 0.065 mg/0.5 mL; SODIUM PHOSPHATE, MONOBASIC, DIHYDRATE 0.023 mg/0.5 mL; PHENOL 1.25 mg/0.5 mL; WATER 0.5 mL/0.5 mL

Typhoid Vi Polysaccharide Vaccine
Typhim Vi®

AHFS Category: 80:12

Typh

Rx only

DESCRIPTION

Typhim Vi®, Typhoid Vi Polysaccharide Vaccine, produced by SanofiWinthrop Industrie , for intramuscular use, is a sterile solution containing the cell surface Vi polysaccharide extracted from Salmonella enterica serovar Typhi, S typhi Ty2 strain. The organism is grown in a semi-synthetic medium. Casein derived raw materials are used early in manufacturing during the fermentation process. The capsular polysaccharide is precipitated from the concentrated culture supernatant by the addition of hexadecyltrimethylammonium bromide, and the product is purified by differential centrifugation and precipitation. Each 0.5 mL dose may contain residual amounts of formaldehyde (not more than 100 mcg) used for the inactivation of the bacterial culture. The potency of the purified polysaccharide is assessed by molecular size and O-acetyl content. Phenol, 0.25%, is added as a preservative. The vaccine contains residual polydimethylsiloxane or fatty-acid ester-based antifoam. The vaccine is a clear, colorless solution. Each dose of 0.5 mL is formulated to contain 25 mcg of purified Vi polysaccharide in a colorless isotonic phosphate buffered saline (pH 7 ± 0.3), 4.150 mg of Sodium Chloride, 0.065 mg of Disodium Phosphate, 0.023 mg of Monosodium Phosphate, and 0.5 mL of Sterile Water for Injection. The vial stopper and the plunger stopper of the syringe are not made with natural rubber latex.

CLINICAL PHARMACOLOGY

Typhoid fever is an infectious disease caused by S typhi. Humans are the only natural host and reservoir for S typhi; infections result from the consumption of food or water that has been contaminated by the excretions of an acute case or a carrier. S typhi organisms efficiently invade the human intestinal mucosae ultimately leading to bacteremia; following a typical 10- to 14-day incubation period, a systemic illness occurs. The clinical presentation of typhoid fever exhibits a broad range of severity and can be debilitating. Classical cases have fever, myalgia, anorexia, abdominal discomfort and headaches; the fever increases step-wise over a period of days and then may remain at 102°F to 106°F over 10 to 14 days before decreasing in a step-wise manner. Skin lesions known as rose spots may be present. Constipation is common in older children and adults, while diarrhea may occur in younger children. Among the less common but most severe complications are intestinal perforation and hemorrhage, and death. The course is typically more severe without appropriate antimicrobial therapy. The case fatality rate was reported to be approximately 10% to 20% in the pre-antibiotic era. (1) (2) (3) During the period of 1983 to 1991 in the US, the case fatality rate reported to the Centers for Disease Control and Prevention (CDC) was 0.2% (9/4010). (4) Infection of the gallbladder can lead to the chronic carrier state.

Typhoid fever is still endemic in many countries of the world where it is predominantly a disease of school-age children and may be a major public health problem. Most cases of typhoid fever in the US are thought to be acquired during foreign travel. During the periods of 1975 to 1984 and 1983 to 1984, respectively, 62% and 70% of the cases of typhoid fever reported to the CDC were acquired during foreign travel; this compares to 33% of cases during 1967-1972. (5)

In 1992, 414 cases of typhoid fever were reported to the CDC. Of these 414 cases, 1 (0.2%) case occurred in an infant under one year of age; 77 (18.6%) cases occurred in persons one to nine years of age; 81 (19.6%) cases occurred in persons 10 to 19 years of age; 251 (60.6%) cases occurred in individuals ≥20 years of age; the age was not available for 4 (1%) cases. One death was reported in 1991. (4) Domestic surveillance could underestimate the risk of typhoid fever in travelers since the disease is unlikely to be reported for persons who received diagnosis and treatment overseas. (6)

Approximately 2% to 4% of acute typhoid fever cases develop into a chronic carrier state. The chronic carrier state occurs more frequently with advanced age, and among females than males. (2) (7) These non-symptomatic carriers are the natural reservoir for S typhi and can serve to maintain the disease in its endemic state or to directly infect new individuals. Outbreaks of typhoid fever are often traced to food handlers who are asymptomatic carriers. (8)

Two formulations were utilized in studies of the Typhoid Vi Polysaccharide Vaccine. These included the liquid formulation which is identical to Typhim Vi vaccine and a lyophilized formulation.

The protective efficacy of each of these formulations of the Typhoid Vi Polysaccharide Vaccine was assessed independently in two trials conducted in areas where typhoid fever is endemic. A single intramuscular dose of 25 mcg was used in these efficacy studies. A randomized double-blind controlled trial with Typhim Vi vaccine (liquid formulation) was conducted in five villages west of Katmandu, Nepal. There were 6,908 vaccinated subjects: 3,454 received Typhim Vi vaccine and 3,454 in the control group received a 23-valent pneumococcal polysaccharide vaccine. Of the 6,908 subjects, 6,439 subjects were in the target population of 5 to 44 years of age. In addition, 165 children ages 2 to 4 years and 304 adults over 44 years of age were included in the study. The overall protective efficacy of Typhim Vi vaccine was 74% (95% confidence interval (CI): 49% to 87%) for blood culture confirmed cases of typhoid fever during 20 months of post-vaccination follow-up. (9) (10) (11)

The protective efficacy of the Typhoid Vi Polysaccharide Vaccine, lyophilized formulation, was evaluated in a randomized double-blind controlled trial conducted in South Africa. There were 11,384 vaccinated children 5 to 15 years of age; 5,692 children received the Vi capsular polysaccharide vaccine and 5,692 in the control group received Meningococcal Polysaccharide (Groups A+C) Vaccine. The protective efficacy for the Vi capsular polysaccharide (lyophilized formulation) group for blood culture confirmed cases of typhoid fever was 55% (95% CI: 30% to 70%) overall during 3 years of post-vaccination follow-up, and was 61%, 52% and 50%, respectively, for years 1, 2, and 3. Vaccination was associated with an increase in anti-Vi antibodies as measured by radioimmunoassay (RIA) and enzyme-linked immunosorbent assay. Antibody levels remained elevated at 6 and 12 months post-vaccination. (11) (12)

Because of the low incidence of typhoid fever, efficacy studies were not feasible in a US population.

Controlled comparative efficacy studies of Typhim Vi vaccine and other types of typhoid vaccines have not been performed.

An increase in serum anti-capsular antibodies is thought to be the basis of protection provided by Typhim Vi vaccine. However, a specific correlation of post-vaccination antibody levels with subsequent protection is not available, and the level of Vi antibody that will provide protection has not been determined. Also, limitations exist for comparing immunogenicity results from subjects in endemic areas, where some subjects have baseline serological evidence of prior S typhi exposure, to naive populations such as most American travelers.

In endemic regions (Nepal, South Africa, Indonesia) where trials were conducted, pre-vaccination geometric mean antibody levels suggest that infection with S typhi had previously occurred in a large percentage of the vaccinees. In these populations, specific antibody levels increased four-fold or greater in 68% to 87.5% of older children and adult subjects following vaccination. For 43 persons 15 to 44 years of age in the Nepal pilot study, geometric mean specific antibody levels pre- and 3 weeks post-vaccination were, respectively, 0.38 and 3.68 mcg antibody/mL by RIA; 79% had a four-fold or greater rise in Vi antibody levels. (9) (12)

Immunogenicity and safety trials were conducted in an adult US population. A single dose of Typhim Vi vaccine induced a four-fold or greater increase in antibody levels in 88% and 96% of this adult population for 2 studies, respectively, following vaccination (see Table 1). (10) (13)

Table 1 (10) (13): Vi ANTIBODY LEVELS IN US ADULTS 18 TO 40 YEARS OF AGE GIVEN TYPHIM Vi VACCINE
 |  | GEOMETRIC MEAN ANTIBODY LEVELS (mcg antibody/mL by RIA)
 | N | Pre | Post (4 weeks) | % ≥4 FOLD INCREASE
 |  | (95% CI) | (95% CI) | (95% CI)
Trial 1 (1 lot) | 54 | 0.16 (0.13 to 0.21) | 3.23 (2.59 to 4.03) | 96% (52/54) (87% to 100%)
Trial 2 (2 lots combined) | 97 | 0.17 (0.14 to 0.21) | 2.86 (2.26 to 3.62) | 88% (85/97) (81% to 94%)

No studies of safety and immunogenicity have been conducted in US children. A double-blind randomized controlled trial evaluating the safety and immunogenicity of Typhim Vi vaccine was performed in 175 Indonesian children. The percentage of 2- to 5-year-old children achieving a four-fold or greater increase in antibody levels at 4 weeks post-vaccination was 96.3% (52/54) (95% CI: 87.3% to 99.6%), and in the study subset of 2-year-old children was 94.4% (17/18) (95% CI: 72.7% to 99.9%). The geometric mean antibody levels (mcg antibody/mL by RIA) for the 2- to 5-year-old children and the subset of 2-year-olds were, respectively, 5.81 (4.36 to 7.77) and 5.76 (3.48 to 9.53). (10) (11)

In the US Reimmunization Study, adults previously immunized with Typhim Vi vaccine in other studies were reimmunized with a 25 mcg dose at 27 or 34 months after the primary dose. Data on antibody response to primary immunization, decline following primary immunization, and response to reimmunization are presented in Table 2. Antibody levels attained following reimmunization at 27 or 34 months after the primary dose were similar to levels attained following the primary immunization. (10) (13) This response is typical for a T-cell independent polysaccharide vaccine in that reimmunization does not elicit higher antibody levels than primary immunization. The safety of reimmunization was also evaluated in this study (see ADVERSE REACTIONS section).

Table 2 (10) (13): US STUDIES IN 18- TO 40-YEAR-OLD ADULTS: KINETICS AND PERSISTENCE OF Vi ANTIBODY [mcg antibody/mL by RIA] RESPONSE TO PRIMARY IMMUNIZATION WITH TYPHIM Vi VACCINE, AND RESPONSE TO REIMMUNIZATION AT 27 OR 34 MONTHS
 | PRE-DOSE 1 | 1 MONTH | 11 MONTHS | 18 MONTHS | 27 MONTHS | 34 MONTHS | 1 MONTH POST-REIMMUNIZATION [Includes available data from all reimmunized subjects (subjects initially randomized to Typhim Vi vaccine, and subjects initially randomized to placebo who received open label Typhim Vi vaccine two weeks later).]
GROUP 1 [Group 1: Reimmunized at 27 months following primary immunization.]
N Level 95% CI | 43 0.19 (0.14-0.26) | 43 3.01 (2.22-4.06) | 39 1.97 (1.31-3.00) | ND [Not Done.] | 43 1.07 [Antibody levels pre-reimmunization.] (0.71-1.62) | ND | 43 3.04 (2.17-4.26)
GROUP 2 [Group 2: Reimmunized at 34 months following primary immunization.]
N Level 95% CI | 12 0.14 (0.11-0.18) | 12 3.78 (2.18-6.56) | ND | 10 1.21 (0.63-2.35) | ND | 12 0.76 (0.37-1.55) | 12 3.31 (1.61-6.77)

Concurrently Administered Vaccines

Concomitant Administration of Typhim Vi and Menactra®, Meningococcal (Groups A, C, Y and W-135) Polysaccharide Diphtheria Toxoid Conjugate Vaccine, Manufactured by Sanofi Winthrop Industrie

In a double-blind, randomized, controlled clinical trial, 945 participants aged 18 through 55 years received Typhim Vi and Menactra vaccines concomitantly (N=469), or Typhim Vi vaccine followed one month later by Menactra vaccine (N=476). Sera were obtained approximately 28 days after each respective vaccination. The antibody response to Typhim Vi vaccine and to Menactra vaccine components were similar between groups.

INDICATIONS AND USAGE

Typhim Vi vaccine is indicated for active immunization for the prevention of typhoid fever caused by S typhi and is approved for use in persons two years of age or older.

Immunization with Typhim Vi vaccine should occur at least two weeks prior to expected exposure to S typhi.

Typhim Vi vaccine is not indicated for routine immunization of individuals in the United States (US). (14)

Selective immunization against typhoid fever is recommended under the following circumstances: 1) travelers to areas where a recognized risk of exposure to typhoid exists, particularly ones who will have prolonged exposure to potentially contaminated food and water, 2) persons with intimate exposure (ie, continued household contact) to a documented typhoid carrier, and 3) workers in microbiology laboratories who frequently work with S typhi. (14)

Typhoid vaccination is not required for international travel, but is recommended for travelers to such areas as Africa, Asia, and Central and South America where there is a recognized risk of exposure to S typhi. Current CDC advisories should be consulted with regard to specific locales. Vaccination is particularly recommended for travelers who will have prolonged exposure to potentially contaminated food and water. However, even travelers who have been vaccinated should use caution in selecting food and water. (15)

There is no evidence to support the use of typhoid vaccine to control common source outbreaks, disease following natural disaster or in persons attending rural summer camps. (14)

An optimal reimmunization schedule has not been established. Reimmunization every two years under conditions of repeated or continued exposure to the S typhi organism is recommended at this time.

For recommended primary immunization and reimmunization see DOSAGE AND ADMINISTRATION section.

Typhim Vi vaccine should not be used to treat a patient with typhoid fever or a chronic typhoid carrier.

CONTRAINDICATIONS

Typhim Vi vaccine is contraindicated in patients with a history of hypersensitivity to any component of this vaccine.

WARNINGS

Allergic reactions have been reported rarely in the post-marketing experience (see ADVERSE REACTIONS section).

The safety and immunogenicity of Typhim Vi vaccine in children under two years of age has not been established. As with other polysaccharide vaccines, the antibody response may be inadequate. The decision whether to vaccinate children under 2 years of age depends upon the risk incurred by the child on the basis of the epidemiological context.

Typhim Vi vaccine provides protection against the risk of infection related to Salmonella typhi, but gives no protection against Salmonella paratyphi A or B, non-S typhi species of Salmonella enterica serovar Typhi, or other bacteria that cause enteric disease.

If the vaccine is used in persons deficient in producing antibodies, whether due to genetic defect, immunodeficiency disease, or immunosuppressive therapy, the expected immune response may not be obtained. This includes patients with asymptomatic or symptomatic HIV-infection, severe combined immunodeficiency, hypogammaglobulinemia, or agammaglobulinemia; altered immune states due to diseases such as leukemia, lymphoma, or generalized malignancy; or an immune system compromised by treatment with corticosteroids, alkylating drugs, antimetabolites or radiation. (16)

As with any vaccine, vaccination with Typhim Vi vaccine may not protect 100% of individuals.

PRECAUTIONS

General

Care is to be taken by the health-care provider for the safe and effective use of Typhim Vi vaccine.

Epinephrine injection (1:1000) must be immediately available following immunization should an anaphylactic or other allergic reaction occur due to any component of the vaccine.

Prior to an injection of any vaccine, all known precautions should be taken to prevent adverse reactions. This includes a review of the patient's history with respect to possible hypersensitivity to the vaccine or similar vaccines.

Acute infection or febrile illness may be reason for delaying use of Typhim Vi vaccine except when, in the opinion of the physician, withholding the vaccine entails a greater risk.

Syncope (fainting) has been reported following vaccination with Typhim Vi. Procedures should be in place to prevent falling injury and manage syncopal reactions.

Safety and immunogenicity data from controlled trials are not available for Typhim Vi vaccine following previous immunization with whole-cell typhoid or live, oral typhoid vaccine (see ADVERSE REACTIONS section).

Information for Vaccine Recipients or Parents/Guardians

Before administration, healthcare providers should inform patients, parents or guardians of the benefits and risks of immunization with Typhim Vi vaccine.

Prior to administration of Typhim Vi vaccine, healthcare providers should ask patients, parents and guardians about the recent health status of the patient to be immunized.

Typhim Vi vaccine is indicated in persons traveling to endemic or epidemic areas. Current CDC advisories should be consulted with regard to specific locales.

Travelers should take all necessary precautions to avoid contact with or ingestion of contaminated food and water.

One dose of vaccine should be given at least 2 weeks prior to expected exposure.

Reimmunization consisting of a single-dose for US travelers every two years under conditions of repeated or continued exposure to the S typhi organism is recommended at this time. (14)

As part of the child's or adult's immunization record, the date, lot number, and manufacturer of the vaccine administered should be recorded. (17)

Drug Interactions

Concomitant Vaccine Administration

Typhim Vi was concomitantly administered with Menactra vaccine in individuals 18 through 55 years of age (see CLINICAL PHARMACOLOGY and ADVERSE REACTIONS).

No studies have been conducted in the US to evaluate interactions or immunological interference between the concurrent use of Typhim Vi vaccine and drugs (including antibiotics and antimalarial drugs), immune globulins or other vaccines (including common travelers vaccines such as tetanus, poliomyelitis, hepatitis A, and yellow fever).

Typhim Vi vaccine must not be mixed with any vaccine in the same syringe. Separate injection sites should be used in case of concomitant administration.

CARCINOGENESIS, MUTAGENESIS, IMPAIRMENT OF FERTILITY

Typhim Vi vaccine has not been evaluated for its carcinogenic potential, mutagenic potential or impairment of fertility.

PREGNANCY

Animal reproduction studies have not been conducted with Typhim Vi vaccine. It is not known whether Typhim Vi vaccine can cause fetal harm when administered to a pregnant woman or can affect reproduction capacity. Typhim Vi vaccine should be given to a pregnant woman only if clearly needed. (14)

When possible, delaying vaccination until the second or third trimester to minimize the possibility of teratogenicity is a reasonable precaution. (18)

NURSING MOTHERS

It is not known whether Typhim Vi vaccine is excreted in human milk. Because many drugs are excreted in human milk, caution should be exercised when Typhim Vi vaccine is administered to a nursing woman.

There is no data on the use of this product in nursing mothers.

PEDIATRIC USE

Safety and effectiveness of Typhim Vi vaccine have been established in children 2 years of age and older. (10) (11) (See DOSAGE AND ADMINISTRATION section.)

For children below the age of 2 years, safety and effectiveness have not been established.

ADVERSE REACTIONS

Adverse event information is derived from clinical trials and worldwide post-marketing experience.

Data From Clinical Trials

Because clinical trials are conducted under widely varying conditions, adverse reactions rates observed in the clinical trials of a vaccine cannot be directly compared to rates in the clinical trials of another vaccine and may not reflect the rates observed in practice. The adverse reaction information from clinical trials does, however, provide a basis for identifying the adverse events that appear to be related to vaccine use and for approximating rates.

Safety of Typhim Vi vaccine, the US licensed liquid formulation, has been assessed in clinical trials in more than 4,000 subjects both in countries of high and low endemicity. In addition, the safety of the lyophilized formulation has been assessed in more than 6,000 individuals. The adverse reactions were predominately minor and transient local reactions. Local reactions such as injection site pain, erythema, and induration almost always resolved within 48 hours of vaccination. Elevated oral temperature, above 38°C (100.4°F), was observed in approximately 1% of vaccinees in all studies. No serious or life-threatening systemic events were reported in these clinical trials. (10) (11)

Adverse reactions from two trials evaluating Typhim Vi vaccine lots in the US (18- to 40-year-old adults) are summarized in Table 3. No severe or unusual side effects were observed. Most subjects reported pain and/or tenderness (pain upon direct pressure). Local adverse experiences were generally limited to the first 48 hours. (10) (11)

Table 3 (10) (11): PERCENTAGE OF 18- TO 40-YEAR-OLD US ADULTS PRESENTING WITH LOCAL OR SYSTEMIC REACTIONS WITHIN 48 HOURS AFTER THE FIRST IMMUNIZATION WITH TYPHIM Vi VACCINE
REACTION | Trial 1 Placebo N = 54 | Trial 1 Typhim Vi vaccine N = 54 (1 Lot) | Trial 2 Typhim Vi vaccine N = 98 (2 Lots combined)
Local
Tenderness | 7 (13.0%) | 53 (98.0%) | 95 (96.9%)
Pain | 4 (7.4%) | 22 (40.7%) | 26 (26.5%)
Induration | 0 | 8 (14.8%) | 5 (5.1%)
Erythema | 0 | 2 (3.7%) | 5 (5.1%)
Systemic
Malaise | 8 (14.8%) | 13 (24.0%) | 4 (4.1%)
Headache | 7 (13.0%) | 11 (20.4%) | 16 (16.3%)
Myalgia | 0 | 4 (7.4%) | 3 (3.1%)
Nausea | 2 (3.7%) | 1 (1.9%) | 8 (8.2%)
Diarrhea | 2 (3.7%) | 0 | 3 (3.1%)
Feverish (subjective) | 0 | 6 (11.1%) | 3 (3.1%)
Fever ≥100°F | 0 | 1 (1.9%) | 0
Vomiting | 0 | 1 (1.9%) | 0

No studies were conducted in US children. Adverse reactions from a trial in Indonesia in children one to twelve years of age are summarized in Table 4. (10) (11) No severe or unusual side effects were observed.

Table 4 (10) (11): PERCENTAGE OF INDONESIAN CHILDREN ONE TO TWELVE YEARS OF AGE PRESENTING WITH LOCAL OR SYSTEMIC REACTIONS WITHIN 48 HOURS AFTER THE FIRST IMMUNIZATION WITH TYPHIM Vi VACCINE
REACTIONS | N = 175
Local
Soreness | 23 (13.0%)
Pain | 25 (14.3%)
Erythema | 12 (6.9%)
Induration | 5 (2.9%)
Impaired Limb Use | 0
Systemic
Feverishness [Subjective feeling of fever.] | 5 (2.9%)
Headache | 0
Decreased Activity | 3 (1.7%)

In the US Reimmunization Study, subjects who had received Typhim Vi vaccine 27 or 34 months earlier, and subjects who had never previously received a typhoid vaccination, were randomized to placebo or Typhim Vi vaccine, in a double-blind study. Safety data from the US Reimmunization Study are presented in Table 5. (10) (11) (13) In this study 5/30 (17%) primary immunization subjects and 10/45 (22%) reimmunization subjects had a local reaction. No severe or unusual side effects were observed. Most subjects reported pain and/or tenderness (pain upon direct pressure). Local adverse experiences were generally limited to the first 48 hours. (10) (11) (13)

Table 5 (10) (11) (13): US REIMMUNIZATION STUDY, SUBJECTS PRESENTING WITH LOCAL AND SYSTEMIC REACTIONS WITHIN 48 HOURS AFTER IMMUNIZATION WITH TYPHIM Vi VACCINE
REACTION | PLACEBO (N = 32) | FIRST IMMUNIZATION (N = 30) | REIMMUNIZATION (N = 45 [At 27 or 34 months following a previous dose given in different studies.])
Local
Tenderness | 2 (6%) | 28 (93%) | 44 (98%)
Pain | 1 (3%) | 13 (43%) | 25 (56%)
Induration | 0 | 5 (17%) | 8 (18%)
Erythema | 0 | 1 (3%) | 5 (11%)
Systemic
Malaise | 1 (3%) | 11 (37%) | 11 (24%)
Headache | 5 (16%) | 8 (27%) | 5 (11%)
Myalgia | 0 | 2 (7%) | 1 (2%)
Nausea | 0 | 1 (3%) | 1 (2%)
Diarrhea | 0 | 0 | 1 (2%)
Feverish (subjective) | 0 | 3 (10%) | 2 (4%)
Fever ≥100°F | 1 (3%) | 0 | 1 (2%)
Vomiting | 0 | 0 | 0

Solicited Injection Site and Systemic Reactions When Given With Menactra Vaccine

The majority (70%-77%) of solicited injection site reactions at the Typhim Vi and at the Menactra injection sites were reported as Grade 1 and resolved within 3 days post-vaccination. The most common systemic reactions were headache (41% when Menactra and Typhim Vi were given concomitantly; 42% when Typhim Vi was given with Placebo, and 33% when Menactra vaccine was given alone one month after Typhim Vi vaccination) and fatigue (38% when Menactra vaccine and Typhim Vi were given concomitantly; 35% when Typhim Vi was given with Placebo, and 27% when Menactra vaccine was given alone one month after Typhim Vi vaccination). Fever ≥40.0°C and seizures were not reported.

Data From Worldwide Post-marketing Experience

In addition to reports in clinical trials, worldwide voluntary adverse events reports received since market introduction of Typhim Vi vaccine are listed below. This list includes serious events and/or events which were included based on severity, frequency of reporting or a plausible causal connection to Typhim Vi vaccine. Because these events were reported voluntarily from a population of uncertain size, it is not possible to reliably estimate their frequency or establish a causal relationship to vaccination.

- Gastrointestinal disorders
  Nausea, vomiting, diarrhea, abdominal pain
- General disorders and administration site condition
  Injection site pain, inflammation, induration, and erythema; lymphadenopathy, fever, asthenia, malaise, flu-like episode
- Immune system disorders
  Anaphylaxis, allergic-type reactions such as pruritus, rash, urticaria, angioedema, difficulty breathing, hypotension; serum sickness
- Musculoskeletal and connective tissue disorders
  Myalgia, arthralgia, cervical pain
- Nervous system disorders
  Syncope with and without convulsions, headache, loss of consciousness, tremor
- Respiratory system disorders
  Asthma

Additional Adverse Events

Post-marketing reports of glomerulonephritis, neutropenia, bilateral retinitis, and polyarthritis have been reported in patients who had also received other vaccines; however, a causal relationship has not been established.

Reporting of Adverse Events

Reporting by parents and patients of all adverse events occurring after vaccine administration should be encouraged. Adverse events following immunization with vaccine should be reported by the health-care provider to the US Department of Health and Human Services (DHHS) Vaccine Adverse Event Reporting System (VAERS). Reporting forms and information about reporting requirements or completion of the form can be obtained from VAERS through a toll-free number 1-800-822-7967 or visit the VAERS website at http//www.vaers.org. (17)

Health-care providers also should report these events to the Pharmocovigilance Department, Sanofi Pasteur Inc., Discovery Drive, Swiftwater, PA 18370, or call 1-800-822-2463.

DOSAGE AND ADMINISTRATION

For intramuscular use only.

Dosage

The immunizing dose for adults and children is a single injection of 0.5 mL.

A reimmunizing dose is 0.5 mL. Reimmunization consisting of a single dose for US travelers every two years under conditions of repeated or continued exposure to the S typhi organism is recommended at this time. (14)

Preparation for Administration

The syringe or vial and its packaging should be inspected prior to use for evidence of leakage, premature activation of the plunger, or a faulty tip seal. If any of these conditions exists, do NOT administer the vaccine.

- Syringe

Picture A: Luer-Lok™ syringe

Step 1: Holding the syringe cap in one hand (avoid holding the syringe plunger or barrel), unscrew the tip cap by twisting it counterclockwise.

Step 2: To attach the needle to the syringe, gently twist the needle clockwise into the syringe until slight resistance is felt.

The syringe is intended for single use only, must not be reused, and must be disposed of properly and promptly following its use.

- Vial

Tear off upper seal of vial cap. Cleanse top of rubber stopper of the vial with a suitable antiseptic.

Use a separate sterile syringe and needle or a sterile disposable unit for each individual patient to prevent the transmission of infectious agents from person to person. Needles should not be recapped and should be properly disposed.

Administration

Parenteral drug products should be inspected visually for particulate matter and discoloration prior to administration, whenever solution and container permit. If any of this conditions exists, do NOT administer the vaccine.

In adults, the intramuscular injection is typically given in the deltoid. In children, the intramuscular injection is given either in the deltoid or the anterolateral thigh.

Do NOT inject this vaccine into the gluteal area or areas where there may be a nerve trunk.

Do NOT inject intravenously.

HOW SUPPLIED

Single-dose syringe, without needle, 0.5 mL, NDC 49281-790-88. Packaged as NDC 49281-790-51.

Multi-dose vial, 20 Dose, NDC 49281-790-38. Packaged as NDC 49281-790-20.

Storage

Store at 2° to 8°C (35° to 46°F). DO NOT FREEZE. Discard if the vaccine has been frozen.

REFERENCES

1 Levine MM, et al. New knowledge on pathogenesis of bacterial enteric infections as applied to vaccine development. Microbiol. Rev. 47: 510-550, 1983
2 Levine MM. Typhoid Fever Vaccines. p 333-361. In Vaccines, Plotkin SA, Mortimer EA, eds. W.B. Saunders, 1988
3 Levine MM, et al. Typhoid Fever Chapter 5, In: Vaccines and Immunotherapy. Stanley J. Cryz, Jr., Editor. pp 59-72, 1991
4 CDC. Summary of Notifiable Diseases, United States 1992. MMWR 41: No. 55, 1993
5 Ryan CA, et al. Salmonella typhi infections in the United States, 1975-1984: Increasing Role of Foreign Travel. Rev Infect Dis 11:1-8, 1989
6 Woodruff BA, et al. A new look at typhoid vaccination. Information for the practicing physician. JAMA 265: 756-759, 1991
7 Ames WR, et al. Age and sex as factors in the development of the typhoid carrier state, and a method for estimating carrier prevalence. Am J Public Health 33: 221-230, 1943
8 CDC. Typhoid fever - Skagit County, Washington. MMWR 39: 749-751, 1990
9 Acharya IL, et al. Prevention of typhoid fever in Nepal with the Vi capsular polysaccharide of Salmonella typhi. N Engl J Med 317: 1101-1104, 1987
10 Unpublished data available from Sanofi Pasteur Inc., compiled 1991
11 Unpublished data available from Sanofi Winthop Industrie
12 Klugman KP, et al. Protective activity of Vi capsular polysaccharide vaccine against typhoid fever. The Lancet, 1165-1169, 1987
13 Keitel WA, et al. Clinical and serological responses following primary and booster immunization with Salmonella typhi Vi capsular polysaccharide vaccines. Vaccines 12: 195-199, 1994
14 Recommendations of the Immunization Practices Advisory Committee (ACIP). Typhoid Immunization. MMWR 43: No. RR-14, 1994
15 CDC. Health Information for International Travel 2001-2002. Atlanta: US Department of Health and Human Services, Public Health Service, 2001
16 ACIP: Use of vaccines and immune globulins in persons with altered immunocompetence. MMWR 42: No. RR-4, 1993
17 CDC. Vaccine Adverse Event Reporting System - United States. MMWR 39: 730-733, 1990
18 ACIP: Update on Adult Immunization. MMWR 40: No. RR-12, 1991

Product Information as of January 2026.

Manufactured by:
SanofiWinthrop Industrie
Marcy L'Etoile, France
US Govt License #1724

Distributed by:
Sanofi Pasteur Inc.
Swiftwater, PA 18370 USA
1-800-VACCINE (1-800-822-2463)

PRINCIPAL DISPLAY PANEL - 0.5 mL Syringe Label

NDC 49281-790-88

Typh
Typhoid Vi
Polysaccharide
Vaccine
Typhim Vi®

single-dose
(0.5 mL)

IM only
Rx only

Sanofi Pasteur

PRINCIPAL DISPLAY PANEL - 0.5 mL Syringe Package

NDC 49281-790-51

Typhoid Vi Polysaccharide Vaccine
Typhim Vi®

Single-dose prefilled syringe

FOR INTRAMUSCULAR ADMINISTRATION.

For indications and directions see enclosed package circular.

Typh

single-dose
prefilled syringe
(0.5 mL)

Rx only

SANOFI PASTEUR

PRINCIPAL DISPLAY PANEL - 20 Dose Vial Label

NDC 49281-790-38

Typhoid Vi
Polysaccharide
Vaccine – Typhim Vi®

Typh

multi-dose
vial
(20 doses)

IM only
For indications and directions see
enclosed package insert.
Store at 2° to 8°C (35° to 46°F).

DO NOT FREEZE. DISCARD IF FROZEN.

Rx only

US Govt License #1724
Manufactured by:
Sanofi Pasteur SA
Lyon France

Distributed by:
Sanofi Pasteur Inc.
Swiftwater, PA 18370 USA
1-800-VACCINE (1-800-822-2463)

Sanofi Pasteur

PRINCIPAL DISPLAY PANEL - 20 Dose Vial Package

NDC 49281-790-20

Typhoid Vi
Polysaccharide Vaccine
Typhim Vi®

Typh

multi-
dose vial
(20 doses)

Rx only

SANOFI PASTEUR